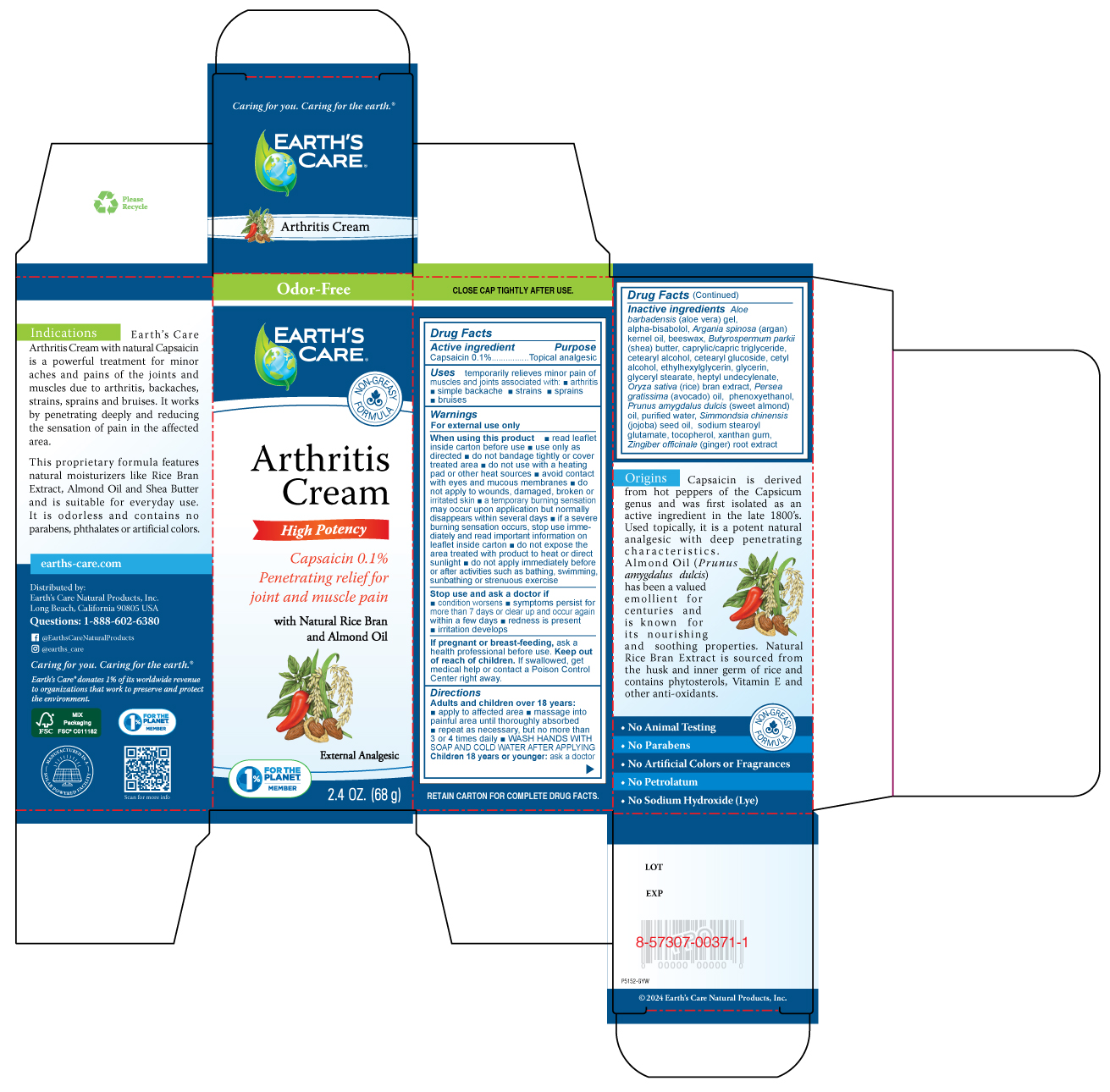 DRUG LABEL: EARTHS CARE ARTHRITIS
NDC: 24286-1559 | Form: CREAM
Manufacturer: DLC Laboratories, Inc.
Category: otc | Type: HUMAN OTC DRUG LABEL
Date: 20250811

ACTIVE INGREDIENTS: CAPSAICIN 0.1 g/100 g
INACTIVE INGREDIENTS: ARGAN OIL; JOJOBA OIL; ALOE VERA LEAF JUICE; CETEARYL ALCOHOL; AVOCADO OIL; SHEA BUTTER; CETEARYL GLUCOSIDE; GLYCERIN; GLYCERYL MONOSTEARATE; HEPTYL UNDECYLENATE; RICE BRAN; PHENOXYETHANOL; ALMOND OIL; WATER; SODIUM STEAROYL GLUTAMATE; XANTHAN GUM; BISABOLOL; CAPRYLIC/CAPRIC TRIGLYCERIDE; WHITE WAX; CETYL ALCOHOL; ETHYLHEXYLGLYCERIN; TOCOPHEROL; GINGER

EARTH'S CARE™ARTHRITIS CREAM

Drug Facts

Active ingredient

Capsaicin 0.1%

Purpose

Topical analgesic

Uses

temporarily relieves minor pain of muscles and joints associated with:

- arthritis
- simple backache
- strains
- sprains
- bruises

Warnings

For external use only

When using this product

- read leaflet inside carton before use
- use only as directed
- do not bandage tightly or cover treated area
- do not use with a heating pad or other heat sources
- avoid contact with eyes and mucous membranes
- do not apply to wounds, damaged, broken or irritated skin
- a temporary burning sensation may occur upon application but normally disappears within several days
- if a severe burning sensation occurs, stop use immediately and read important information on leaflet inside carton
- do not expose the area treated with product to heat or direct sunlight
- do not apply immediately before or after activities such as bathing, swimming, sunbathing or strenuous exercise

Stop use and ask a doctor if

- condition worsens
- symptoms persist for more than 7 days or clear up and occur again within a few days
- redness is present
- irritation develops

PREGNANCY OR BREAST FEEDING

If pregnant or breast-feeding,ask a health professional before use.

Keep out of reach of children.If swallowed, get medical help or contact a Poison Control Center right away.

Directions

Adults and children over 18 years:

- apply to affected area
- massage into painful area until thoroughly absorbed
- repeat as necessary, but no more than 3 or 4 times daily
- WASH HANDS WITH SOAP AND COLD WATER AFTER APPLYING

Children 18 years or younger:ask a doctor

Inactive ingredients

aloe barbadensis (aloe vera) gel, alpha-bisabolol, argania spinosa (argan) kernel oil, beeswax, Butyrospermum parkii(shea) butter, caprylic/capric triglyceride, cetearyl alcohol, cetearyl glucoside, cetyl alcohol, ethylhexylglycerin, glycerin, glyceryl stearate, heptyl undecylenate, Oryza sativa(rice) bran extract, Persea gratissima (avocado) oil, phenoxyethanol, Prunus amygdalus dulcis(sweet almond) oil, purified water, Simmondsia chinensis (jojoba) seed oil, sodium stearoyl glutamate, tocopherol, xanthan gum, Zingiber officinale (ginger) root extract

Questions

1-888-602-6380

Distributed by:
Earth's Care Natural Products, Inc.
Long Beach, California 90805 USA

PRINCIPAL DISPLAY PANEL - 68 g Tube Box

Odor-Free

EARTH'S
CARE ™

NON-GREASY
FORMULA

Arthritis
Cream

High Potency

Capsaicin 0.1%
Penetrating relief for
joint and muscle pain

with Natural Rice Bran
and Almond Oil

External Analgesic

1%
FOR THE
PLANET ℠
MEMBER

2.4 OZ. (68 g)